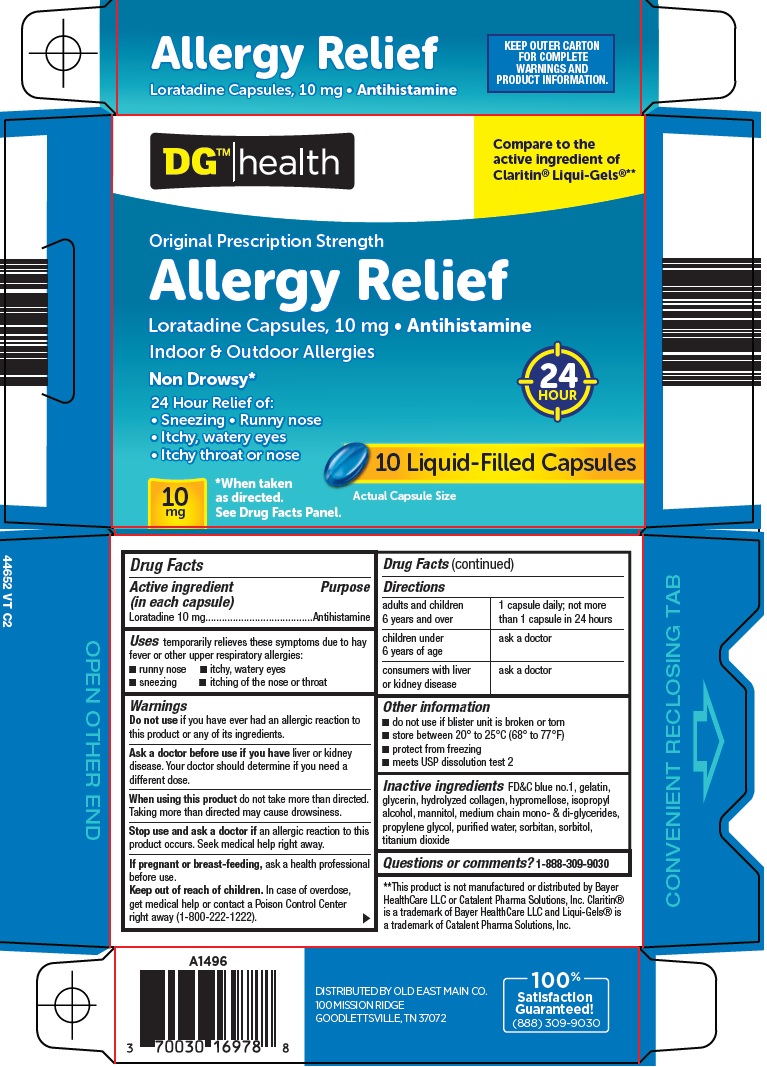 DRUG LABEL: dg health allergy relief
NDC: 55910-629 | Form: CAPSULE, LIQUID FILLED
Manufacturer: Dolgencorp Inc
Category: otc | Type: HUMAN OTC DRUG LABEL
Date: 20250311

ACTIVE INGREDIENTS: LORATADINE 10 mg/1 1
INACTIVE INGREDIENTS: FD&C BLUE NO. 1; GELATIN, UNSPECIFIED; GLYCERIN; HYPROMELLOSE, UNSPECIFIED; ISOPROPYL ALCOHOL; MANNITOL; GLYCERYL MONO- AND DICAPRYLOCAPRATE; PROPYLENE GLYCOL; WATER; SORBITAN; SORBITOL; TITANIUM DIOXIDE

Dolgencorp, LLC Allergy Relief Drug Facts

Active ingredient (in each capsule)

Loratadine 10 mg

Purpose

Antihistamine

Uses

temporarily relieves these symptoms due to hay fever or other upper respiratory allergies:

- runny nose
- itchy, watery eyes
- sneezing
- itching of the nose or throat

Warnings

Do not use

if you have ever had an allergic reaction to this product or any of its ingredients.

Ask a doctor before use if you have

liver or kidney disease. Your doctor should determine if you need a different dose.

When using this product

do not take more than directed. Taking more than directed may cause drowsiness.

Stop use and ask a doctor if

an allergic reaction to this product occurs. Seek medical help right away.

If pregnant or breast-feeding,

ask a health professional before use.

Keep out of reach of children.

In case of overdose, get medical help or contact a Poison Control Center right away (1-800-222-1222).

Directions

adults and children 6 years and over | 1 capsule daily; not more than 1 capsule in 24 hours
children under 6 years of age | ask a doctor
consumers with liver or kidney disease | ask a doctor

Other information

- do not use if blister unit is broken or torn
- store between 20° to 25°C (68° to 77°F)
- protect from freezing
- meets USP dissolution test 2

Inactive ingredients

FD&C blue no.1, gelatin, glycerin, hydrolyzed collagen, hypromellose, isopropyl alcohol, mannitol, medium chain mono- & di-glycerides, propylene glycol, purified water, sorbitan, sorbitol, titanium dioxide

Questions or comments?

1-888-309-9030

Package/Label Principal Display Panel

DGTM | health

Compare to the active ingredient of Claritin® Liqui-Gels®

Original Prescription Strength

Allergy Relief

Loratadine Capsules, 10 mg • Antihistamine

Indoor & Outdoor Allergies

Non Drowsy*

24 HOUR

24 Hour Relief of:

• Sneezing • Runny nose

• Itchy, watery eyes

• Itchy throat or nose

10 Liquid-Filled Capsules

10 mg

*When taken as directed. See Drug Facts Panel.

Actual Capsule Size